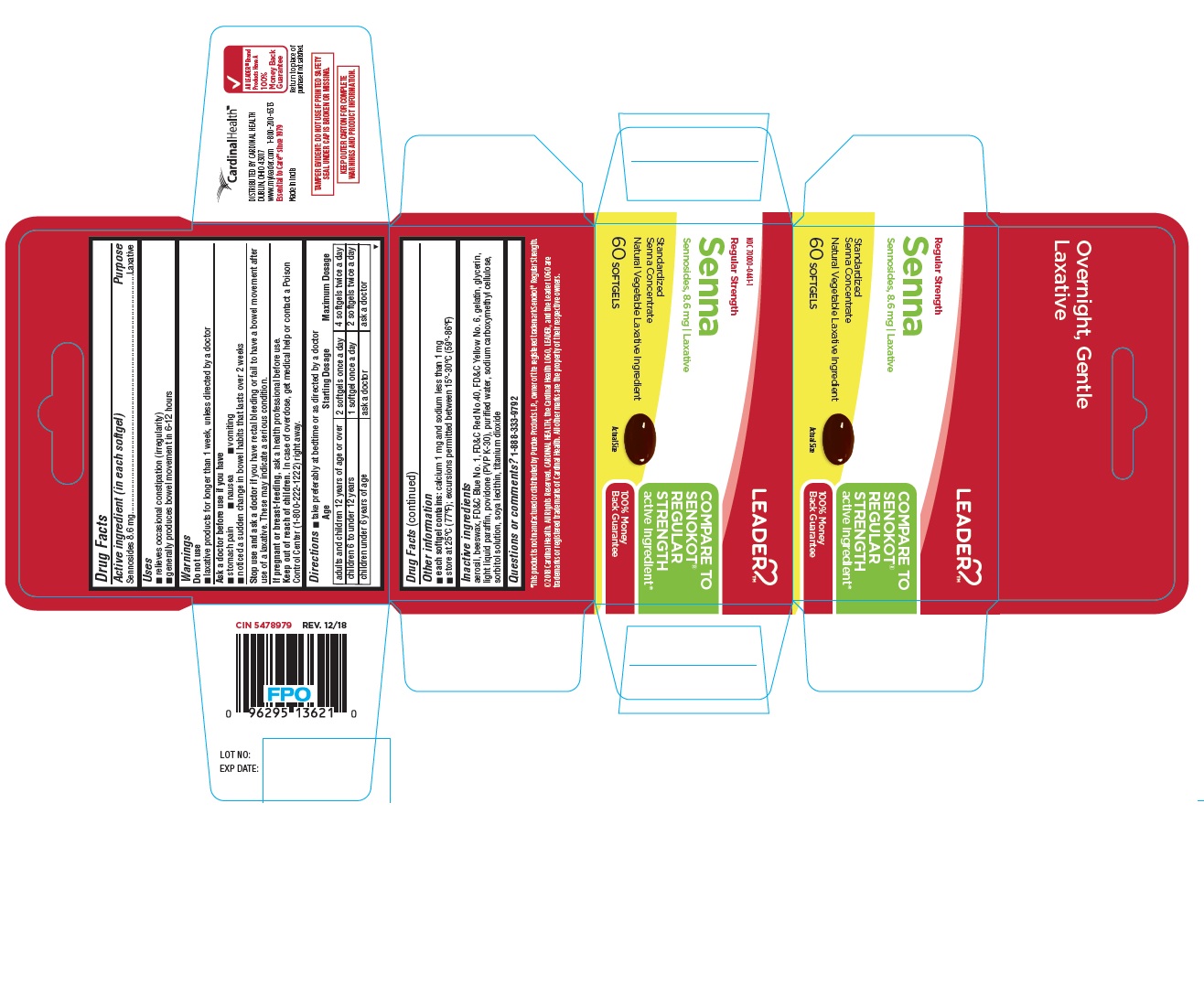 DRUG LABEL: SENNA
NDC: 70000-0441 | Form: CAPSULE, GELATIN COATED
Manufacturer: Cardinal Health
Category: otc | Type: HUMAN OTC DRUG LABEL
Date: 20250818

ACTIVE INGREDIENTS: SENNOSIDES 8.6 mg/1 1
INACTIVE INGREDIENTS: SILICA DIMETHYL SILYLATE; YELLOW WAX; FD&C BLUE NO. 1; FD&C RED NO. 40; FD&C YELLOW NO. 6; GELATIN; GLYCERIN; PARAFFIN; POVIDONE K30; WATER; CARBOXYMETHYLCELLULOSE SODIUM; SORBITOL; LECITHIN, SOYBEAN; TITANIUM DIOXIDE

LEADER™ REGULAR STRENGTH SENNA 60CT

Drug Facts

Active ingredient (in each softgel)

Sennosides 8.6 mg

Purpose

Laxative

Uses

■ relieves occasional constipation (irregularity)
■ generally produces bowel movement in 6-12 hours

Warnings

Do not use

■ laxative products for longer than 1 week, unless directed by a doctor

Ask a doctor before use if you have

■ stomach pain ■ nausea ■ vomiting
■ noticed a sudden change in bowel habits that lasts over 2 weeks

Stop use and ask a doctor if you have rectal bleeding or fail to have a bowel movement after
use of a laxative. These may indicate a serious condition.

PREGNANCY OR BREAST FEEDING

If pregnant or breast-feeding,ask a health professional before use.

Keep out of reach of children. In case of overdose, get medical help or contact a Poison
Control Center (1-800-222-1222) right away.

Directions

■ take preferably at bedtime or as directed by a doctor

Age | Starting Dosage | Maximum Dosage
adults and children 12 years of age or over | 2 softgels once a day | 4 softgels twice a day
children 6 to under 12 years | 1 softgel once a day | 2 softgels twice a day
children under 6 years of age | ask a doctor | ask a doctor

Drug Facts (continued)

Other information

■ each softgel contains: calcium 1 mg and sodium less than 1 mg
■ store at 25ºC (77ºF); excursions permitted between 15º-30ºC (59º-86ºF)

Inactive ingredients

aerosil, beeswax, FD&C Blue No. 1, FD&C Red No.40, FD&C Yellow No. 6, gelatin, glycerin,
light liquid paraffin, povidone (PVP K-30), purified water, sodium carboxymethyl cellulose,
sorbitol solution, soya lecithin, titanium dioxide

Questions or comments? 1-888-333-9792

PRINCIPAL DISPLAY PANEL - LEADER™ REGULAR STRNGTH SENNA 60 Softgels Bottle Carton

LEADER

COMPARE TO
SENOKOT®
REGULAR
STRENGTH
active ingredient*
100% Money
Back Guarantee

NDC 70000-0441-1

Regular Strength

Senna

Sennosides, 8.6 mg | Laxative

Standardized
Senna Concentrate
Natural Vegetable Laxative Ingredient

60 SOFTGELS

Actual Size

*This product is not manufactured or distributed by Purdue Products L.P., owner of the registered trademark Senokot® Regular Strength.